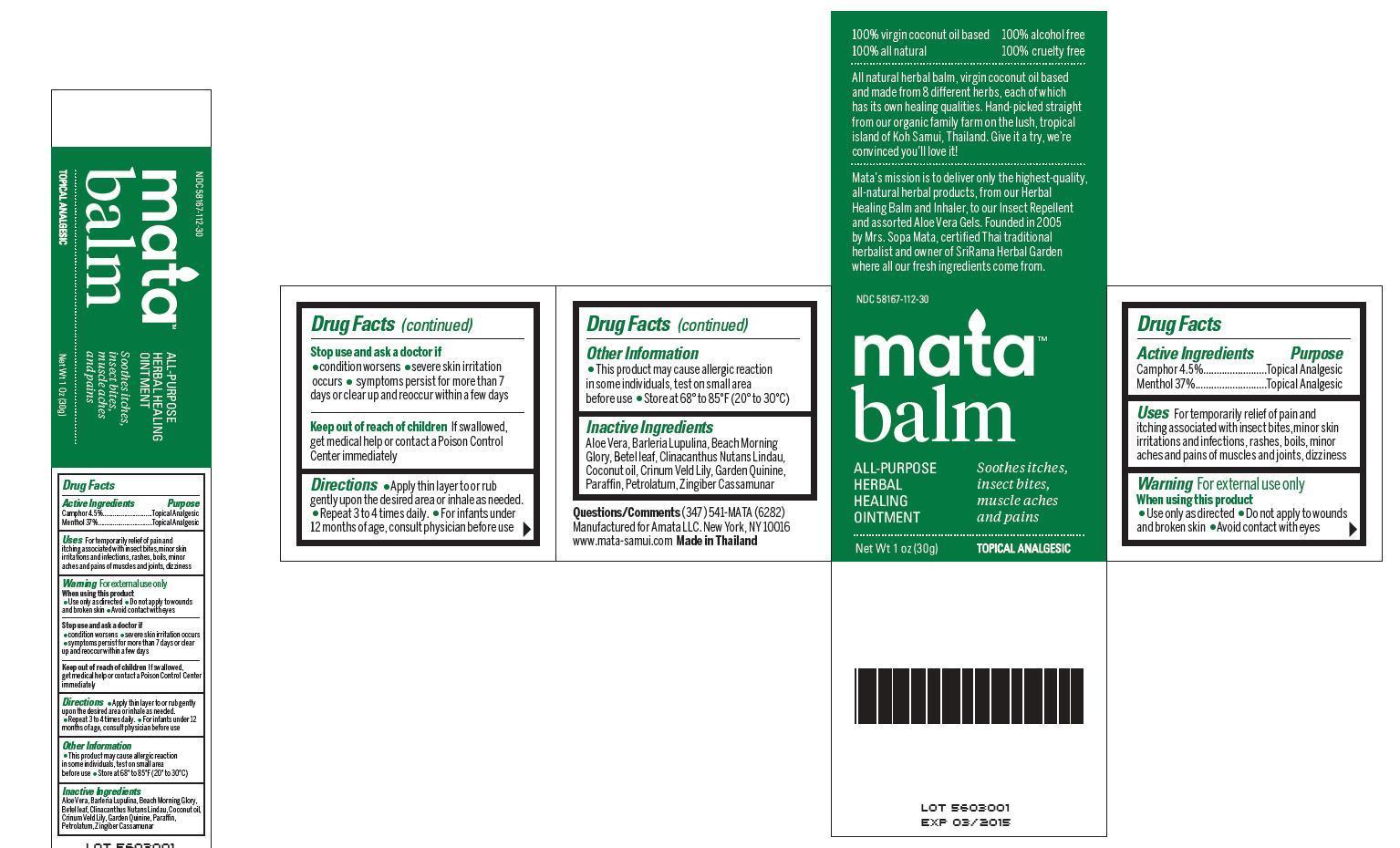 DRUG LABEL: Mata Balm
NDC: 58167-112 | Form: OINTMENT
Manufacturer: Amata LLC
Category: otc | Type: HUMAN OTC DRUG LABEL
Date: 20130511

ACTIVE INGREDIENTS: CAMPHOR (NATURAL) 45 mg/1 g; MENTHOL 367 mg/1 g
INACTIVE INGREDIENTS: ALOE VERA LEAF; BARLERIA PRIONITIS WHOLE; IPOMOEA PES-CAPRAE FLOWERING TOP; PIPER BETLE LEAF; CAJANUS CAJAN LEAF; COCONUT OIL; QUININE; PARAFFIN; PETROLATUM; ZINGIBER MONTANUM FLOWERING TOP; CRINUM ASIATICUM WHOLE

Drug Facts

Active Ingredient

Camphor 4.5%

Menthol 37%

Purpose

Topical Analgesic

Keep out of reach of children

If swallowed, get medical help or contact a Poison Control Center immediately.

Uses

For temporarily relief of pain and itching associated with insect bites,minor skin irritations and infections,

rashes, boils, minor aches and pains of muscles and joints, dizziness

Warnings

For external use only

When using this product

- Use only as directed
- Do not apply to wounds and broken skin
- Avoid contact with eyes

Stop use and ask a doctor if

- condition worsens
- severe skin irritation occurs
- symptoms persist for more than 7 days or clear up and reoccur within a few days

Directions

Apply thin layer to or rub gently upon the desired area or inhale as needed. Repeat 3 to 4 times daily. For infants under 12 months of age, consult physician before use

Inactive Ingredients

Aloe Vera, Barleria Lupulina, Beach Morning Glory, Betel leaf, Clinacanthus Nutans Lindau, Coconut oil, Crinum Veld Lily, Garden Quinine, Paraffin, Petrolatum,Zingiber Cassamunar.

Other Information:

This product may cause allergic reaction in some individuals, test on small area before use

Store at 68° to 85°F (20° to 30°C)